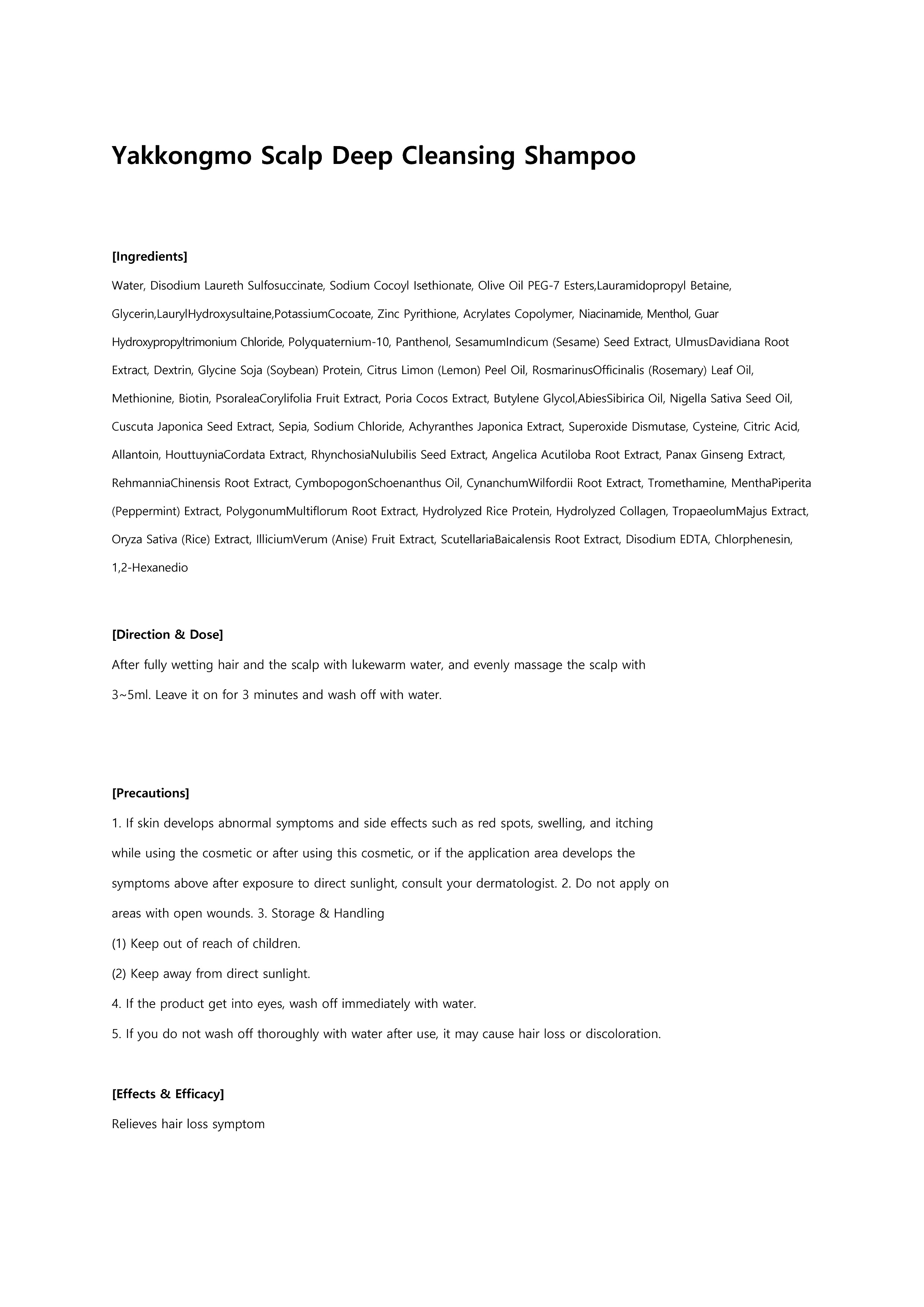 DRUG LABEL: Yakkongmo scalp deep cleansingshampoo
NDC: 73540-001 | Form: SHAMPOO
Manufacturer: BOBSNU CO., LTD.
Category: otc | Type: HUMAN OTC DRUG LABEL
Date: 20200222

ACTIVE INGREDIENTS: NIACINAMIDE 0.3 g/100 mL; BIOTIN 0.06 g/100 mL; PYRITHIONE ZINC 2 g/100 mL; DEXPANTHENOL 0.5 g/100 mL
INACTIVE INGREDIENTS: WATER

ACTIVE INGREDIENT

zinc pyrithione, dexpanthenol, niacinamide, biotin

INACTIVE INGREDIENT

Water, Butylene Glycol, Glycerin, Betaine, Hydrolyzed Jojoba Esters, 1,2-Hexanediol,Carbomer,CaprylylGlycol,CentellaAsiatica Extract,Allantoin,Hydroxyethylcellulose,IlliciumVerum (Anise) Fruit Extract, Panthenol,Disodium EDTA,PunicaGranatum Fruit Extract,FicusCarica (Fig) Fruit Extract,Morus Alba Fruit Extract, Ginkgo Biloba Nut Extract, Glycine, Serine, GlutamicAcid,Brassica OleraceaItalica (Broccoli) Extract,Medicago Sativa (Alfalfa) Extract,Brassica OleraceaCapitata (Cabbage) Leaf extract,TriticumVulgare (Wheat) Germ Extract,Hydrolyzed Collagen,Pentylene Glycol,AsparticAcid,Leucine,Brassica Campestris (Rapeseed) Extract,RaphanusSativus (Radish) Seed Extract,Alanine,Lysine,Arginine,Tyrosine,Phenylalanine, Threonine,Proline,Valine,Isoleucine,Histidine, SodiumPhosphate,Tryptophan,Asparagine,Cysteine,Glutamine,Methionine,sh-Oligopeptide-1,sh-Oligopeptide-2,sh-Polypeptide-1

PURPOSE

Relieves hair loss symptom

WARNINGS

1. If skin develops abnormal symptoms and side effects such as red spots, swelling, and itching

while using the cosmetic or after using this cosmetic, or if the application area develops the symptoms above after exposure to direct sunlight, consult your dermatologist. 2. Do not apply on areas with open wounds. 3. Storage & Handling

(1) Keep out of reach of children.

(2) Keep away from direct sunlight.

4. If the product get into eyes, wash off immediately with water.

5. If you do not wash off thoroughly with water after use, it may cause hair loss or discoloration.

Keep Out of Reach of Children

Uses

Helps skin brightening and anti-wrinkle.

Directions

After fully wetting hair and the scalp with lukewarm water, and evenly massage the scalp with 3~5ml. Leave it on for 3 minutes and wash off with water.